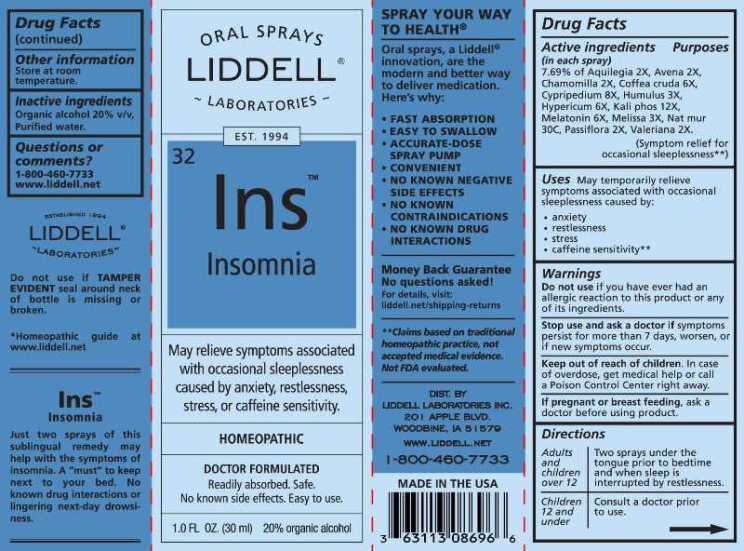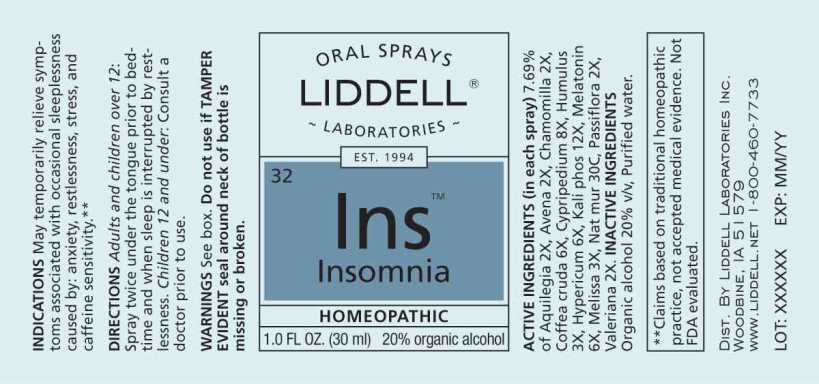 DRUG LABEL: Insomnia
NDC: 50845-0272 | Form: SPRAY
Manufacturer: Liddell Laboratories, Inc.
Category: homeopathic | Type: HUMAN OTC DRUG LABEL
Date: 20231031

ACTIVE INGREDIENTS: AQUILEGIA VULGARIS 2 [hp_X]/1 mL; AVENA SATIVA FLOWERING TOP 2 [hp_X]/1 mL; MATRICARIA CHAMOMILLA WHOLE 2 [hp_X]/1 mL; ARABICA COFFEE BEAN 6 [hp_X]/1 mL; CYPRIPEDIUM PARVIFLORUM VAR. PUBESCENS ROOT 8 [hp_X]/1 mL; HOPS 3 [hp_X]/1 mL; HYPERICUM PERFORATUM WHOLE 6 [hp_X]/1 mL; DIBASIC POTASSIUM PHOSPHATE 12 [hp_X]/1 mL; MELATONIN 6 [hp_X]/1 mL; MELISSA OFFICINALIS WHOLE 3 [hp_X]/1 mL; SODIUM CHLORIDE 30 [hp_C]/1 mL; PASSIFLORA INCARNATA FLOWERING TOP 2 [hp_X]/1 mL; VALERIAN 2 [hp_X]/1 mL
INACTIVE INGREDIENTS: WATER; ALCOHOL

DRUG FACTS:

ACTIVE INGREDIENTS:

(in each spray) 7.69% of Aquilegia Vulgaris 2X, Avena Sativa 2X, Chamomilla 2X, Coffea Cruda 6X, Cypripedium Pubescens 8X, Humulus Lupulus 3X, Hypericum Perforatum 6X, Kali Phosphoricum 12X, Melatonin 6X, Melissa Officinalis 3X, Natrum Muriaticum 30C, Passiflora Incarnata 2X, Valeriana Officinalis 2X.

USES:

May temporarily relieve symptoms associated with occasional sleeplessness caused by:

anxiety, restlessness, stress, and caffeine sensitivity**
**Claims based on traditional homeopathic practice, not accepted medical evidence. Not FDA evaluated.

WARNINGS:

See box.

Do not use if you have ever had an allergic reaction to this product or any of its ingredients.

Stop use and ask a doctor if symptoms persist for more than 7 days, worsen, or if new symptoms occur.

Keep out of reach of children. In case of overdose, get medical help or call a Poison Control Center right away.

If pregnant or breast feeding, ask a doctor before using product.

Do not use if TAMPER EVIDENT seal around neck of bottle is missing or broken.

Store at room temperature.

Keep out of reach of children. In case of overdose, get medical help or call a Poison Control Center right away.

DIRECTIONS:

Adults and children over 12: Two sprays under the tongue prior to bedtime and when sleep is interrupted by restlessness.

Children under 12: Consult a doctor prior to use.

USES:

May temporarily relieve symptoms associated with occasional sleeplessness caused by:

anxiety, restlessness, stress, and caffeine sensitivity**
**Claims based on traditional homeopathic practice, not accepted medical evidence. Not FDA evaluated.

INACTIVE INGREDIENTS:

Organic alcohol 20% v/v, Purified water.

QUESTIONS:

DIST. BY:

LIDDELL LABORATORIES INC.

201 APPLE BLVD.

WOODBINE, IA 51579

WWW.LIDDELL.NET

1-800-460-7733

PACKAGE LABEL DISPLAY:

ORAL SPRAYS

LIDDELL
LABORATORIES

EST. 1994

32 Ins
Insomnia

May relieve symptoms associated
with occasional sleeplessness
caused by anxiety, restlessness,
stress, or caffeine sensitivity.

HOMEOPATHIC
DOCTOR FORMULATED

Readily absorbed. Safe.
No known side effects. Easy to use.

1.0 FL OZ (30 ml)